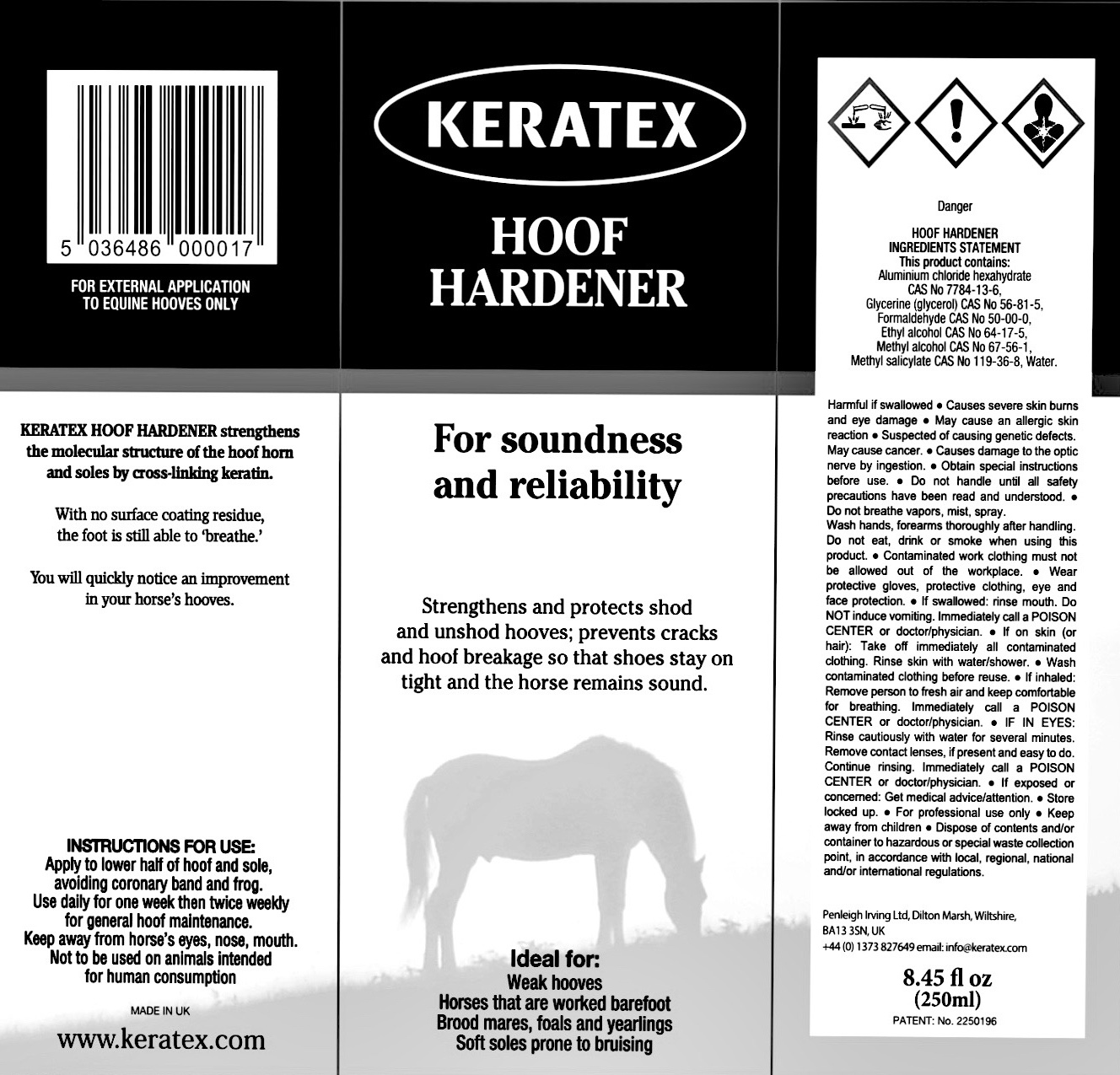 DRUG LABEL: Keratex
NDC: 27426-040 | Form: Liquid
Manufacturer: Penleigh Irving Ltd
Category: animal | Type: OTC ANIMAL DRUG LABEL
Date: 20250611

ACTIVE INGREDIENTS: ALUMINUM CHLORIDE 0.408 g/1.675 mL; GLYCERIN 0.211 g/1.675 mL; FORMALDEHYDE 0.068 g/1.675 mL; ALCOHOL 0.065 g/1.675 mL; METHYL ALCOHOL 0.003 g/1.675 mL

Penleigh Irving Ltd.

Dilton Marsh, Wiltshire, BK13 3SN, UK

+44 (0) 1373 827649 email: info@keratex.com

www.keratex.com

PACKAGE LABEL

Keratex Hoof Hardener

For soundness and reliability

Strengthens and protects shod and unshod hooves; prevents cracks and hoof breakage so that shoes stay on tight and the horse remains sound.

Ideal for: Weak hooves. Horses that are worked barefoot. Brood mares, foals and yearlings. Soft soles prone to bruising.

Keratex Hoof Hardener strengthens the molecular structure of the hoof horn and soles by cross-linking keratin. With no surface coating residue, the foot is still able to ‘breathe’. You will quickly notice an improvement in your horse’s hooves.

Instructions For Use: Apply to the lower half of the hoof and sole, avoiding coronary band and frog. Use daily for one week then twice weekly for general maintenance.

Keep away from horse's eyes, nose and mouth. Not to be used on animals intended for human consumption. For external application to equine hooves only.

Harmful if swallowed. Causes severe skin burns and eye damage. May cause an allergic skin reaction. Suspected of causing genetic defects. May cause cancer. Causes damage to the optic nerve by ingestion. Obtain special instructions before use. Do not handle until all safety precautions have been read and understood. Do not breathe vapors, mist spray. Wash hands, forearms thoroughly after handling. Do not eat drink, smoke when using this product. Contaminated work clothing must not be allowed out of the workplace. Wear protective gloves, protective clothing, eye and face protection. If swallowed: rinse mouth. Do NOT induce vomiting. Immediately call a POISON CENTER or doctor/physician. If on skin (or hair): Take off immediately all contaminated clothing. Rinse skin with water/shower. Wash contaminated clothing before reuse. If inhaled: Remove person to fresh air and keep comfortable for breathing. Immediately call a POISON CENTER or doctor/physician. IF IN EYES: Rinse cautiously with water for several minutes: Remove contact lenses, if present and easy to do. Continue rinsing. Immediately call a POISON CENTER or doctor/physician. If exposed or concerned: Get medical advice/attention. Store locked up. For professional use only. Keep away from children. Dispose of contents and/or container to hazardous or special waste collection point, in accordance with local, regional, national and/or international regulations.

Hoof Hardener Ingredients Statement. This product contains: Aluminium chloride hexahydrate CAS No. 7784-13-6. Glycerine (glycerol) CAS No. 56-81-5. Formaldehyde CAS No. 50-00-0. Ethyl alcohol CAS No. 64-17-5. Methyl alcohol CAS No. 67-56-1. Methyl salicylate CAS No. 119-36-8. Water.

Patent: No. 2250196

8.45 fl oz (250ml)